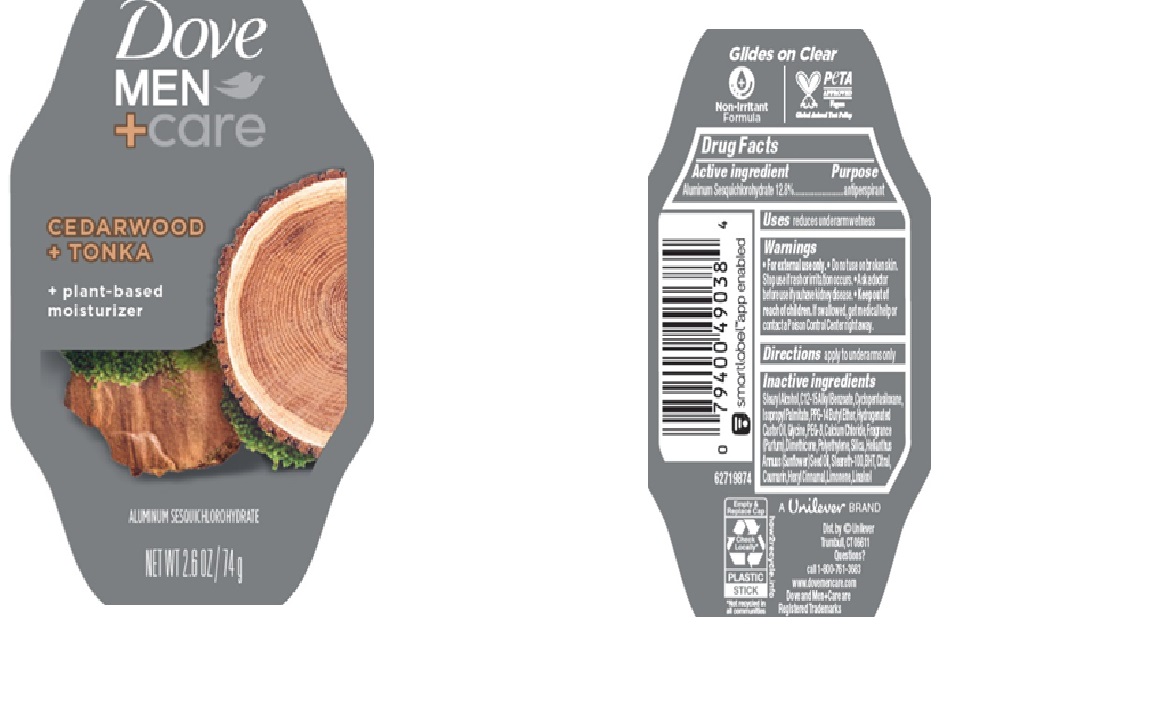 DRUG LABEL: Dove
NDC: 64942-2356 | Form: STICK
Manufacturer: Conopco d/b/a/ Unilever
Category: otc | Type: HUMAN OTC DRUG LABEL
Date: 20250331

ACTIVE INGREDIENTS: ALUMINUM SESQUICHLOROHYDRATE 12.8 g/100 g
INACTIVE INGREDIENTS: LINALOOL, (+/-)-; C12-15 ALKYL BENZOATE; HYDROGENATED CASTOR OIL; STEARETH-100; BHT; STEARYL ALCOHOL; CITRAL; COUMARIN; HEXYL CINNAMAL; LIMONENE, (+)-; PEG-8; SILICA; POLYETHYLENE; PPG-14 BUTYL ETHER; ISOPROPYL PALMITATE; HELIANTHUS ANNUUS (SUNFLOWER) SEED OIL; CALCIUM CHLORIDE; GLYCINE; CYCLOPENTASILOXANE; DIMETHICONE

Dove Men + Care Cedarwood + Tonka 72H Antiperspirant

DESCRIPTION

Dove Men + Care Cedarwood + Tonka 72H Antiperspirant

ACTIVE INGREDIENT

Aluminum Sesquichlorohydrate (12.8)

PURPOSE

antiperspirant

INDICATIONS AND USAGE

reduces underarm wetness

WARNINGS

For external use only.

Do not use on broken skin.

Ask a doctor before use if you have kidney disease.

Stop use if rash or irritation occurs.

Keep out of reach of children. If swallowed, get medical help or contact a Poison Control Center right away.

DOSAGE AND ADMINISTRATION

apply to underarms only

INACTIVE INGREDIENT

Stearyl Alcohol,C12 -15 Alkyl Benzoate,Cyclopentasiloxane, Isopropyl Palmitate,PPG -14 Butyl Ether,Hydrogenated Castor Oil,Glycine,PEG -8,Calcium Chloride,Fragrance (Parfum),Dimethicone,Polyethylene,Silica,Helianthus Annuus(Sunflower)Seed Oil,Steareth-100,BHT,Citral, Coumarin,Hexyl Cinnamal,Limonene,Linalool